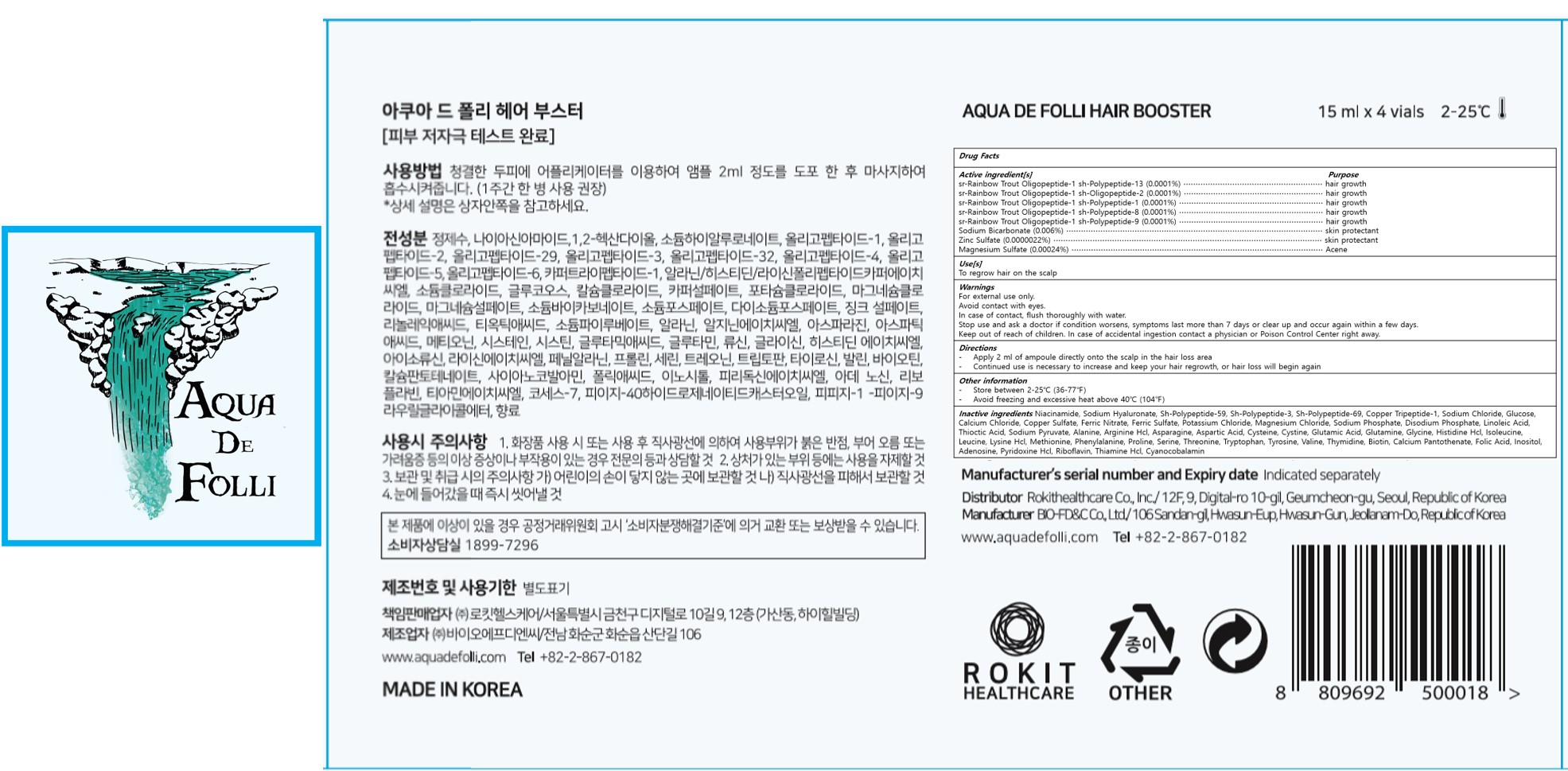 DRUG LABEL: AQUA DE FOLLI HAIR BOOSTER
NDC: 80592-202 | Form: LIQUID
Manufacturer: ROKIT HEALTHCARE Inc.
Category: otc | Type: HUMAN OTC DRUG LABEL
Date: 20201005

ACTIVE INGREDIENTS: MAGNESIUM SULFATE, UNSPECIFIED 0.00024 g/100 mL; SODIUM BICARBONATE 0.006 g/100 mL; ZINC SULFATE 0.0000022 g/100 mL
INACTIVE INGREDIENTS: LEUCINE; LYSINE HYDROCHLORIDE; METHIONINE; SERINE; THREONINE; TRYPTOPHAN; BIOTIN; CALCIUM PANTOTHENATE; NIACINAMIDE; RIBOFLAVIN; THIAMINE HYDROCHLORIDE; COCETH-7; PPG-1-PEG-9 LAURYL GLYCOL ETHER; BECAPLERMIN; SODIUM CHLORIDE; CALCIUM CHLORIDE; FERRIC SULFATE; SODIUM PHOSPHATE, DIBASIC, ANHYDROUS; THIOCTIC ACID; SODIUM PYRUVATE; ALANINE; CYSTINE; GLYCINE; ISOLEUCINE; PREZATIDE COPPER; WATER; 1,2-HEXANEDIOL; FIBROBLAST GROWTH FACTOR 7; ANHYDROUS DEXTROSE; CUPRIC SULFATE; POTASSIUM CHLORIDE; MAGNESIUM CHLORIDE; ASPARTIC ACID; SODIUM PHOSPHATE; PHENYLALANINE; PROLINE; HYALURONATE SODIUM; HUMAN TYPE III COLLAGEN; FERRIC NITRATE; LINOLEIC ACID; ARGININE HYDROCHLORIDE; ASPARAGINE; INOSITOL; TYROSINE; VALINE; FOLIC ACID; ADENOSINE; PYRIDOXINE HYDROCHLORIDE; CYANOCOBALAMIN; POLYOXYL 40 HYDROGENATED CASTOR OIL; HISTIDINE MONOHYDROCHLORIDE; CYSTEINE; GLUTAMIC ACID; GLUTAMINE; THYMIDINE

80592-202

Active ingredient[s]

sr-Rainbow Trout Oligopeptide-1 sh-Polypeptide-13 (0.0001%)

sr-Rainbow Trout Oligopeptide-1 sh-Oligopeptide-2 (0.0001%)

sr-Rainbow Trout Oligopeptide-1 sh-Polypeptide-1 (0.0001%)

sr-Rainbow Trout Oligopeptide-1 sh-Polypeptide-8 (0.0001%)

sr-Rainbow Trout Oligopeptide-1 sh-Polypeptide-9 (0.0001%)

Sodium Bicarbonate (0.006%)

Zinc Sulfate (0.0000022%)

Magnesium Sulfate (0.00024%)

Purpose

Hair growth

Skin protectant

Acene

Use[s]

To regrow hair on the scalp

Warnings

For external use only.

Avoid contact with eyes.

In case of contact, flush thoroughly with water.

Warnings

Stop use and ask a doctor if condition worsens, symptoms last more than 7 days or clear up and occur again within a few days.

Warnings

Keep out of reach of children. In case of accidental ingestion contact a physician or Poison Control Center right away.

Directions

- Apply 2ml of ampoule directly onto the scalp in the hair loss area

- Continued use is necessary to increase and keep your hair regrowth, or hair loss will begin again

Other information

- Store between 2-25℃ (36-77℉)
- Avoid freezing and excessive heat above 40℃ (104℉)

Inactive ingredients

1,2-Hexanediol, Niacinamide, Sodium Hyaluronate, Sh-Polypeptide-59, Sh-Polypeptide-3, Sh-Polypeptide-69, Copper Tripeptide-1, Sodium Chloride, Glucose, Calcium Chloride, Copper Sulfate, Ferric Nitrate, Ferric Sulfate, Potassium Chloride, Magnesium Chloride, Sodium Phosphate, Disodium Phosphate, Linoleic Acid, Thioctic Acid, Sodium Pyruvate, Alanine, Arginine Hcl, Asparagine, Aspartic Acid, Cysteine, Cystine, Glutamic Acid, Glutamine, Glycine, Histidine Hcl, Isoleucine, Leucine, Lysine Hcl, Methionine, Phenylalanine, Proline, Serine, Threonine, Tryptophan, Tyrosine, Valine, Thymidine, Biotin, Calcium Pantothenate, Folic Acid, Inositol, Adenosine, Pyridoxine Hcl, Riboflavin, Thiamine Hcl, Cyanocobalamin, Coceth-7, PEG-40 Hydrogenated Castor Oil, PPG-1-PEG-9 Lauryl Glycol Ether